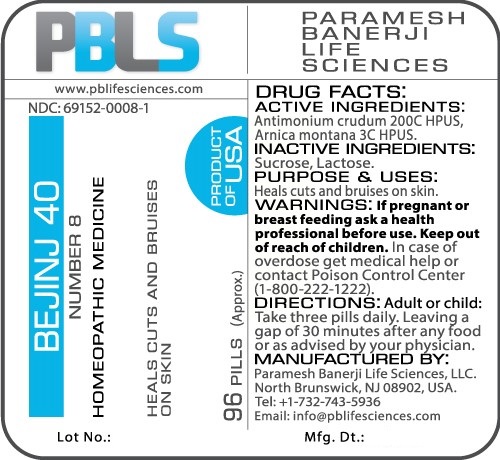 DRUG LABEL: Bejinj 40 (Number 8)
NDC: 69152-0008 | Form: PELLET
Manufacturer: Paramesh Banerji Life Sciences LLC
Category: homeopathic | Type: HUMAN OTC DRUG LABEL
Date: 20161109

ACTIVE INGREDIENTS: ANTIMONY TRISULFIDE 200 [hp_C]/1 1; ARNICA MONTANA 3 [hp_C]/1 1
INACTIVE INGREDIENTS: SUCROSE; LACTOSE

DRUG FACTS: Active Ingredients

Antimonium crudum 200C HPUS, Arnica montana 3C HPUS

Inactive Ingredients

Sucrose, Lactose

Purpose

Heals cuts and bruises on skin

Uses

Heals cuts and bruises on skin

Warnings

If pregnant or breast feeding ask a health professional before use.

Keep out of reach of children. In case of overdose, get medical help or contact a Poison Control Center (1-800-222-1222) right away.

Direction

Adult or child: Take three pills daily. Leaving a gap of 30 minutes after any food or as advised by your physician.

Manufactured by

Paramesh Banerji Life Sciences, LLC.

North Brunswick, NJ 08902, USA.

Tel: +1-732-743-5936

Email: info@pblifesciences.com

Principal Display Panel

NDC: 69152-0008-1

Bejinj 40

Number 8

Homeopathic Medicine

Heals cuts and bruises on skin

96 pills (Approx.)

Product of USA